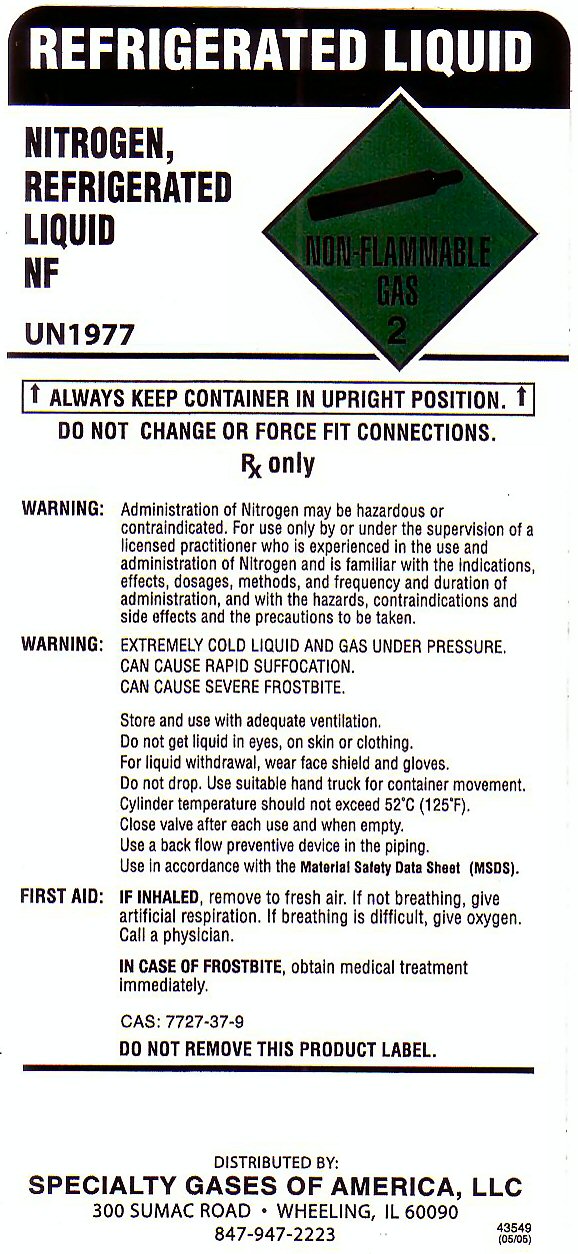 DRUG LABEL: NITROGEN
NDC: 59754-002 | Form: GAS
Manufacturer: Specialty Gases of America LLC
Category: prescription | Type: HUMAN PRESCRIPTION DRUG LABEL
Date: 20111103

ACTIVE INGREDIENTS: NITROGEN 99 L/100 L

NITROGEN REFRIGERATED LIQUID NF LABEL

REFRIGERATED LIQUID NITROGEN REFRIGERATED LIQUID NF NON-FLAMMABLE GAS-2 UN1977 ALWAYS KEEP CONTAINER IN UPRIGHT POSITION. DO NOT CHANGE OR FORCE FIT CONNECTIONS
Rx ONLY
WARNING: ADMINISTRATION OF NITROGEN MAY BE HAZARDOUS OR CONTRAINDICATED. FOR USE ONLY BY OR UNDER THE SUPERVISION OF A LICENSED PRACTITIONER WHO IS EXPERIENCED IN THE USE AND ADMINISTRATION OF NITROGEN AND IS FAMILIAR WITH THE INDICATIONS, EFFECTS, DOSAGES, METHODS, AND FREQUENCY AND DURATION OF ADMINISTRATION AND WITH THE HAZARDS, CONTRAINDICATIONS AND SIDE EFFECTS AND THE PRECAUTIONS TO BE TAKEN.
WARNING: EXTREMELY COLD LIQUID AND GAS UNDER PRESSURE. CAN CAUSE RAPID SUFFOCATION. CAN CAUSE SEVERE FROSTBITE STORE AND USE WITH ADEQUATE VENTILATION. DO NOT GET LIQUID IN EYES, ON SKIN OR CLOTHING. FOR LIQUID WITHDRAWAL, WEAR FACE SHIELD AND GLOVES. DO NOT DROP. USE SUITABLE HAND TRUCK FOR CONTAINER MOVEMENT. CYLINDER TEMPERATURE SHOULD NOT GET ABOVE 52 C (125 F) CLOSE VALVE AFTER EACH USE AND WHEN EMPTY. USE A BACK FLOW PREVENTATIVE DEVICE IN THE PIPING. USE IN ACCORDANCE WITH THE MATERIAL SAFETY DATA SHEET (MSDS)
FIRST AID: IN INHALED, REMOVE TO FRESH AIR. IF NOT BREATHING, GIVE ARTIFICIAL RESPIRATION. IF BREATHING DIFFICULT, GIVE OXYGEN. CALL A PHYSICIAN. IN CASE OF FROSTBITE OBTAIN MEDICAL TREATMENT IMMEDIATELY.
CAS: 7727-37-9 DO NOT REMOVE THIS PRODUCT LABEL.